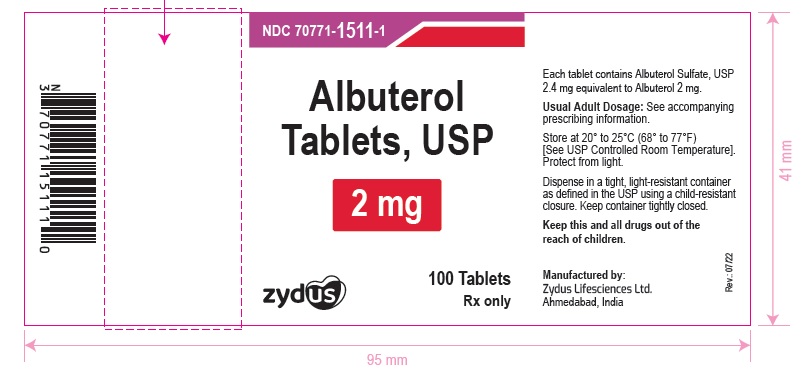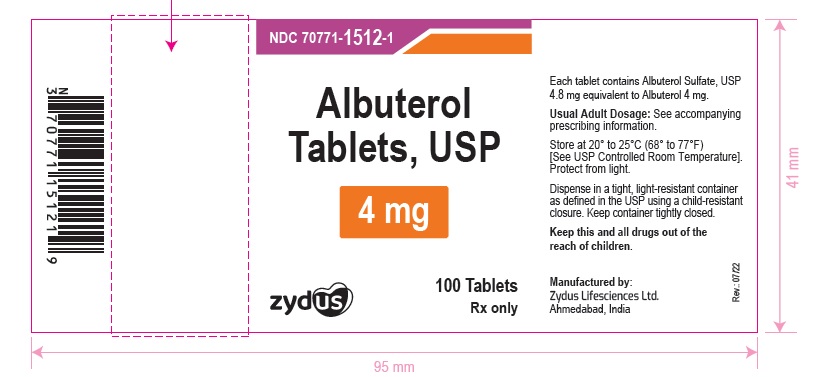 DRUG LABEL: Albuterol
NDC: 70771-1511 | Form: TABLET
Manufacturer: Zydus Lifesciences Limited
Category: prescription | Type: HUMAN PRESCRIPTION DRUG LABEL
Date: 20241125

ACTIVE INGREDIENTS: ALBUTEROL SULFATE 2 mg/1 1
INACTIVE INGREDIENTS: LACTOSE MONOHYDRATE; MAGNESIUM STEARATE; MICROCRYSTALLINE CELLULOSE; POVIDONE K30; SILICON DIOXIDE; SODIUM STARCH GLYCOLATE TYPE A POTATO; STARCH, CORN

Albuterol Tablets, USP

PACKAGE LABEL.PRINCIPAL DISPLAY PANEL

NDC 70771-1511-1 in bottle of 100 tablets

Albuterol tablets USP, 2 mg

Rx only

100 Tablets

NDC 70771-1512-1 in bottle of 100 tablets

Albuterol tablets USP, 4 mg

Rx only

100 Tablets